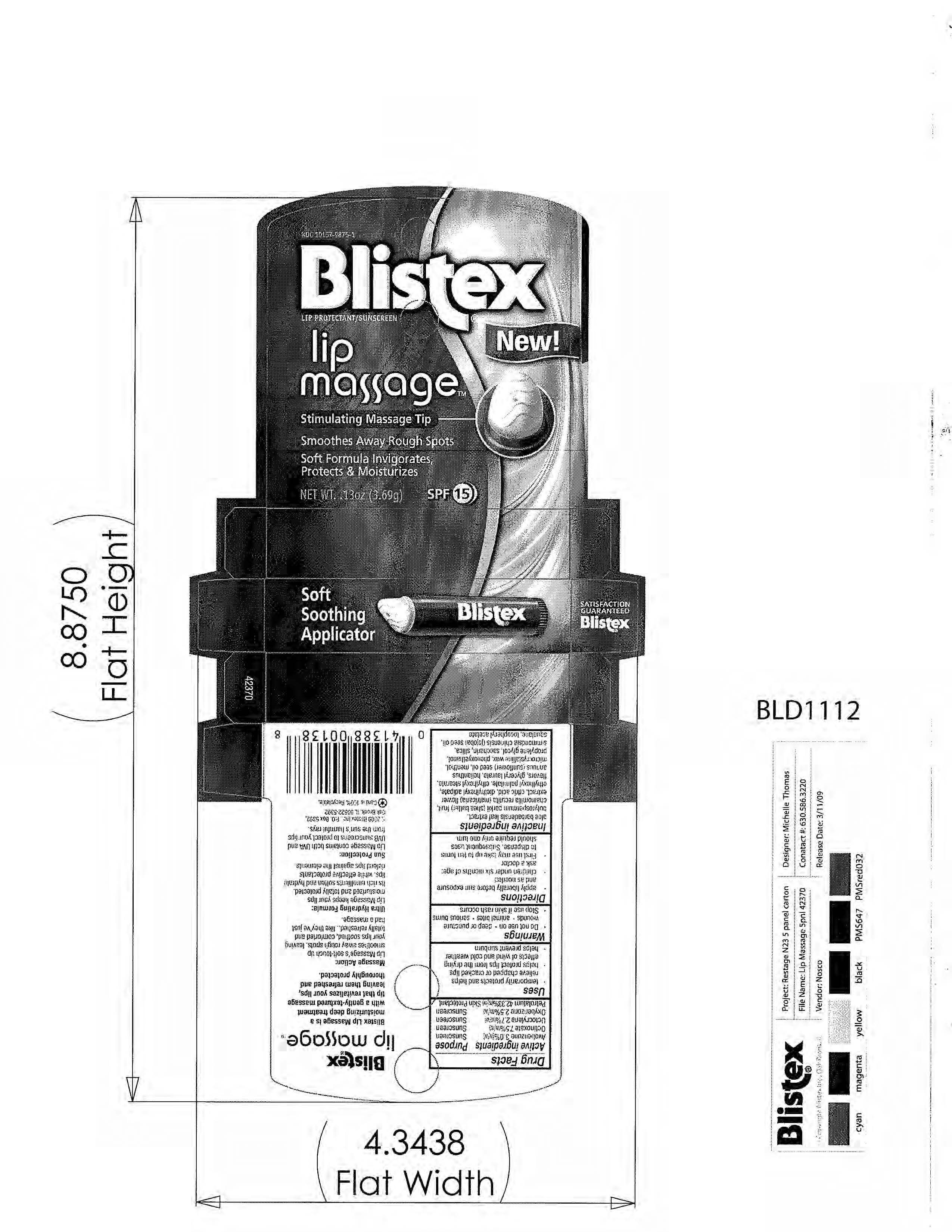 DRUG LABEL: Blistex
NDC: 10157-9875 | Form: GEL
Manufacturer: Blistex Inc
Category: otc | Type: HUMAN OTC DRUG LABEL
Date: 20091215

ACTIVE INGREDIENTS: PETROLATUM 43.33 g/1 1; OCTINOXATE 7.5 g/1 1; AVOBENZONE 3.0 g/1 1; OCTOCRYLENE 2.7 g/1 1; OXYBENZONE 2.5 g/1 1

DRUG FACTS

ACTIVE INGREDIENT

Avobenzone 3.0%

Octinoxate 7.5%

Octocrylene 2.7%

Oxybenzone 2.5%

Petrolatum 42.33

PURPOSE

SKIN PROTECTANT

SUNSCREEN

- Temporarily protects and helps relieve chapped or cracked lips
- Helps protect lips from the drying effects of wind and cold weather
- Helps prevent sunburn

WHEN USING

- Apply liberally before sun exposure and as needed
- First use may take up to ten turns to dispense, subsequent uses should require only one turn

- Do not use on deep or puncture wounds
- animal bites
- serious burns
- Stop use if skin rash occurs
- Children under six months of age ask a doctor

PACKAGE LABEL

Blistex Lip Massage

Lip Protector/ Sunscreen

Smooths away Rough Spots

Soft formula invigorates, protects and moisturizers

SPF15